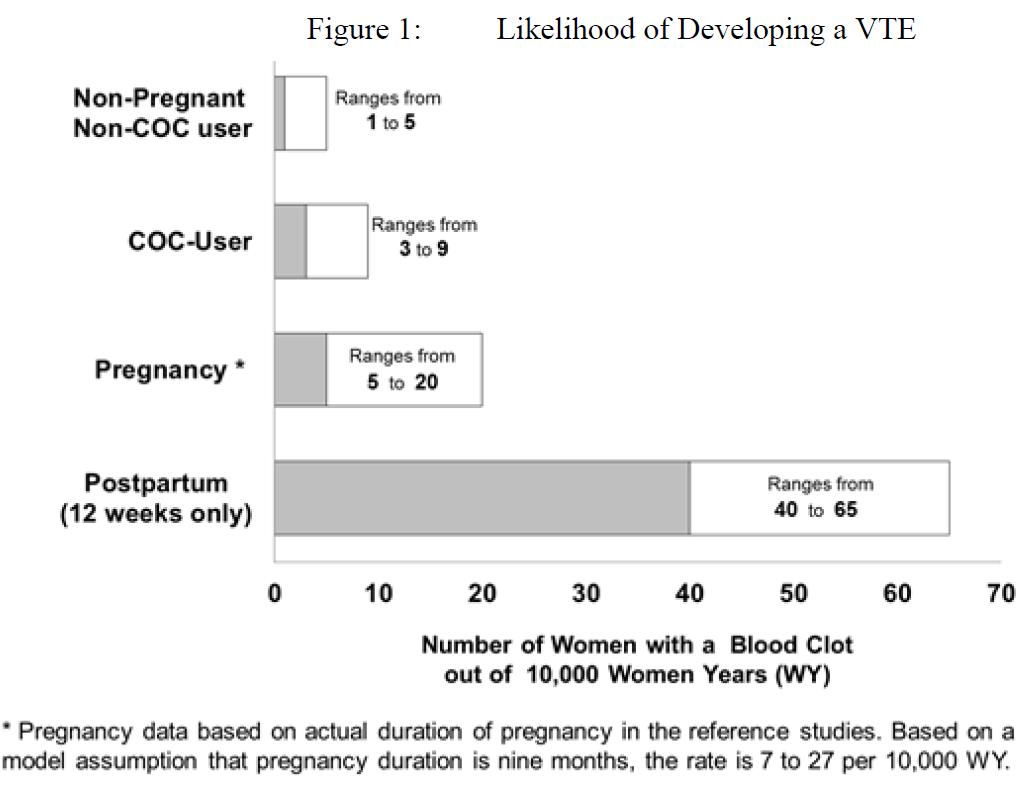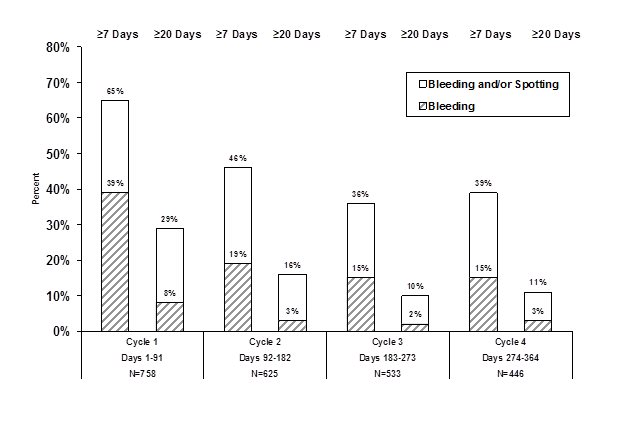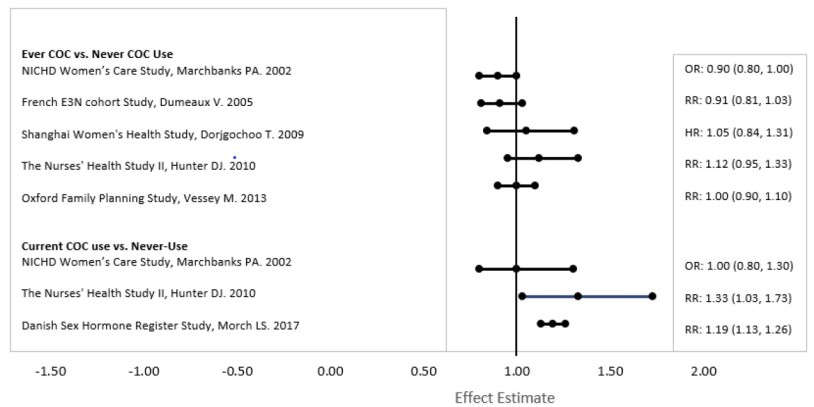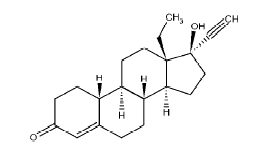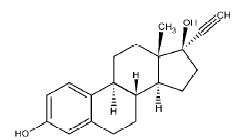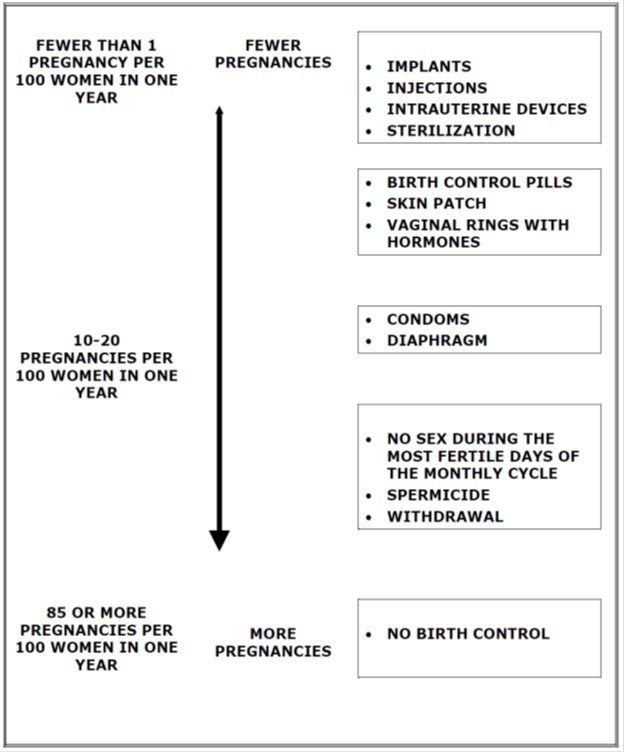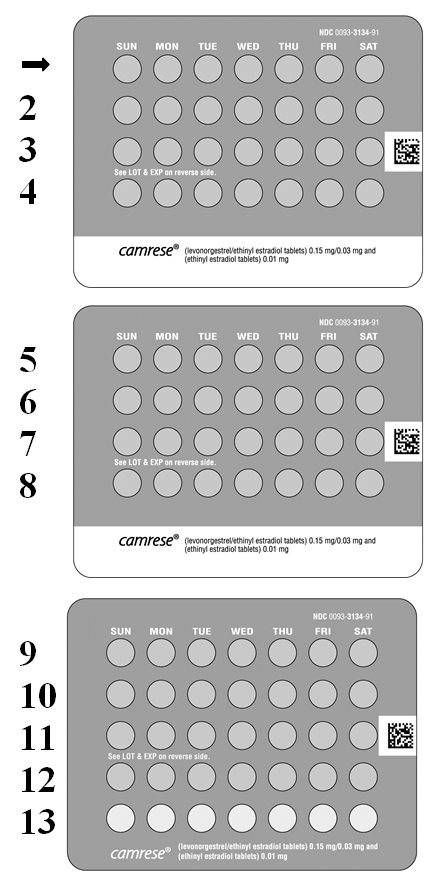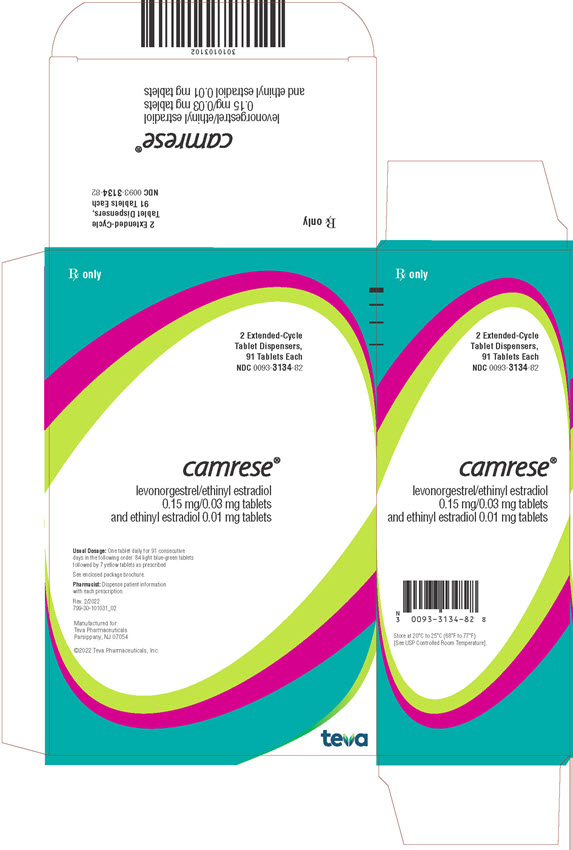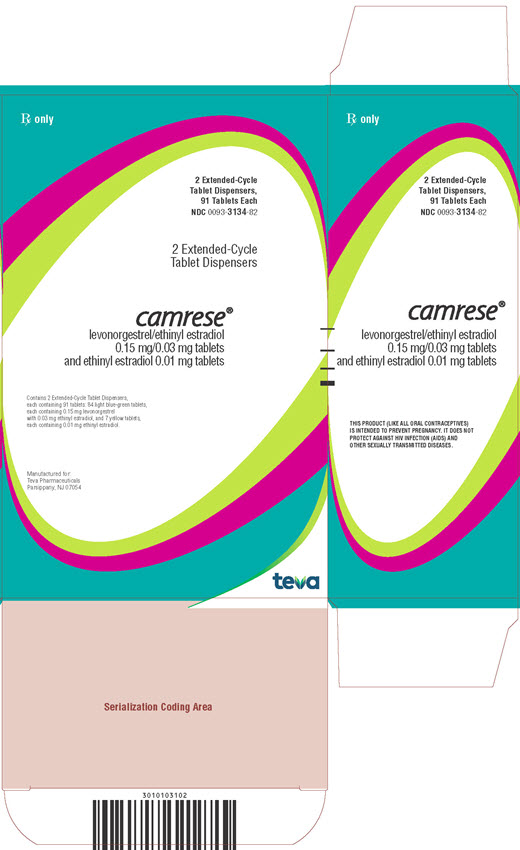 DRUG LABEL: Camrese
NDC: 0093-3134 | Form: KIT | Route: ORAL
Manufacturer: Teva Pharmaceuticals USA, Inc.
Category: prescription | Type: HUMAN PRESCRIPTION DRUG LABEL
Date: 20241025

ACTIVE INGREDIENTS: LEVONORGESTREL 0.15 mg/1 1; ETHINYL ESTRADIOL 0.03 mg/1 1; ETHINYL ESTRADIOL 0.01 mg/1 1
INACTIVE INGREDIENTS: ANHYDROUS LACTOSE; D&C YELLOW NO. 10; FD&C BLUE NO. 1; FD&C YELLOW NO. 6; HYPROMELLOSE 2208 (3 MPA.S); HYPROMELLOSE 2910 (15 MPA.S); LACTOSE MONOHYDRATE; MAGNESIUM STEARATE; MICROCRYSTALLINE CELLULOSE; TITANIUM DIOXIDE; TRIACETIN; POLYDEXTROSE; ANHYDROUS LACTOSE; D&C YELLOW NO. 10; FD&C YELLOW NO. 6; HYPROMELLOSE 2910 (3 MPA.S); HYPROMELLOSE 2910 (6 MPA.S); MAGNESIUM STEARATE; MICROCRYSTALLINE CELLULOSE; POLACRILIN POTASSIUM; POLYETHYLENE GLYCOL 400; POLYSORBATE 80; TITANIUM DIOXIDE; POLYDEXTROSE

HIGHLIGHTS OF PRESCRIBING INFORMATION

These highlights do not include all the information needed to use CAMRESE safely and effectively. See full prescribing information for CAMRESE.
CAMRESE® (levonorgestrel and ethinyl estradiol tablets; ethinyl estradiol tablets) for oral use
Initial U.S. Approval: 1982

WARNING: CIGARETTE SMOKING AND SERIOUS CARDIOVASCULAR EVENTS

See full prescribing information for complete boxed warning.

- CAMRESE is contraindicated in women over 35 years old who smoke.
- Cigarette smoking increases the risk of serious cardiovascular events from combination oral contraceptive (COC) use.

1 INDICATIONS AND USAGE

CAMRESE is a combination of levonorgestrel, a progestin, and ethinyl estradiol, an estrogen, indicated for use by females of reproductive potential to prevent pregnancy. (1)

2 DOSAGE AND ADMINISTRATION

Take one tablet daily by mouth at the same time every day for 91 days in the order directed on the blister pack. (2)

3 DOSAGE FORMS AND STRENGTHS

CAMRESE consists of 84 light blue-green tablets containing 0.15 mg levonorgestrel and 0.03 mg ethinyl estradiol, and 7 yellow tablets containing 0.01 mg ethinyl estradiol. (3)

4 CONTRAINDICATIONS

- A high risk of arterial or venous thrombotic diseases (4)
- Undiagnosed abnormal uterine bleeding (4)
- Breast cancer (4)
- Liver tumors or liver disease, acute viral hepatitis or decompensated cirrhosis (4)
- Co-administration with Hepatitis C drug combinations containing ombitasvir/paritaprevir/ritonavir, with or without dasabuvir.(4)

5 WARNINGS AND PRECAUTIONS

- Vascular risks: Stop if a thrombotic or thromboembolic event occurs. Stop at least 4 weeks before and through 2 weeks after major surgery. Start no earlier than 4 weeks after delivery, in women who are not breastfeeding. Consider cardiovascular risk factors before initiating in all females, particularly those over 35 years. (5.1, 5.5)
- Liver disease: Discontinue if jaundice occurs. (5.2)
- Hypertension: If used in females with well-controlled hypertension, monitor blood pressure and stop if blood pressure rises significantly. (5.3)
- Gallbladder disease: May cause or worsen gallbladder disease. (5.6)
- Adverse carbohydrate and lipid metabolic effects: Monitor glucose in prediabetic and diabetic women taking CAMRESE. Consider an alternate contraceptive method for women with uncontrolled dyslipidemias. (5.7)
- Headache: Evaluate significant change in headaches and discontinue if indicated. (5.8)
- Uterine bleeding: May cause irregular bleeding or amenorrhea. Evaluate for other causes if symptoms persist. (5.9)

6 ADVERSE REACTIONS

The most common adverse reactions (≥5%) in clinical trials for CAMRESE are irregular and/or heavy uterine bleeding, weight gain, and acne. (6)

To report SUSPECTED ADVERSE REACTIONS, contact Teva Pharmaceuticals at 1-888-483-8279 or FDA at 1-800-FDA-1088 or www.fda.gov/medwatch.

7 DRUG INTERACTIONS

Enzyme inducers (e.g., CYP3A4): May decrease the effectiveness of CAMRESE or increase breakthrough bleeding. Counsel patients to use a backup method or alternative method of contraception when enzyme inducers are used with CAMRESE. (7.1)

8 USE IN SPECIFIC POPULATIONS

- Pregnancy: Discontinue if pregnancy occurs. (8.1)
- Lactation: Advise use of another method; CAMRESE is not recommended for nursing mothers; may decrease milk production. (8.2)

FULL PRESCRIBING INFORMATION

WARNING: CIGARETTE SMOKING AND SERIOUS CARDIOVASCULAR EVENTS

Cigarette smoking increases the risk of serious cardiovascular events from combination oral contraceptives (COC) use. This risk increases with age, particularly in women over 35 years of age, and with the number of cigarettes smoked. For this reason, COCs, including CAMRESE, are contraindicated in women who are over 35 years of age and smoke. [See Contraindications (4) and Warnings and Precautions (5.1)].

1 INDICATIONS AND USAGE

CAMRESE® is indicated for use by females of reproductive potential to prevent pregnancy.

2 DOSAGE AND ADMINISTRATION

2.1 How to Start and Take CAMRESE

Begin CAMRESE on the first Sunday after the onset of menstruation. If menstruation begins on a Sunday, take the first light blue-green tablet that day.

For each 91-day course, take in the following order:

1. Start the first light blue-green tablet on the first Sunday after onset of menstruation. Then take one light blue-green tablet daily for 84 consecutive days. Use a non-hormonal backup method of contraception (such as condoms and spermicide) until a light blue-green tablet has been taken daily for 7 consecutive days.

2. Then take one yellow tablet for 7 consecutive days. Bleeding should occur during the 7 days that the yellow tablets are taken.

Begin the next and all subsequent 91-day cycles without interruption on the same day of the week (Sunday) on which the patient began her first dose of CAMRESE, following the same schedule: 84 days taking a light blue-green tablet followed by 7 days taking a yellow tablet. If the patient does not immediately start her next pill pack, instruct her to protect herself from pregnancy by using a non-hormonal backup method of contraception until she has taken a light blue-green tablet daily for 7 consecutive days.

Switching to CAMRESE from another oral hormonal contraceptive or from another contraceptive method (transdermal patch, vaginal ring, injection, intrauterine contraceptive, implant)

Start on the Sunday after the patient’s next period starts. Use additional non-hormonal contraceptive (such as condoms and spermicide) until the patient has taken a light blue-green tablet for 7 consecutive days.

Starting CAMRESE after Abortion or Miscarriage

First-trimester

CAMRESE may be started on the Sunday after an abortion or miscarriage. The patient must use additional non-hormonal contraception (such as condoms and spermicide) until the patient has taken a light blue-green tablet for 7 consecutive days.

Second-trimester

Do not start until 4 weeks after a second-trimester abortion or miscarriage, due to the increased risk of thromboembolic disease. Start contraceptive therapy with CAMRESE following the instructions for women not currently using hormonal contraception. Use additional non-hormonal contraception (such as condoms and spermicide) until the patient has taken a light blue-green tablet for 7 consecutive days [see Contraindications (4) and Warnings and Precautions (5.1)].

Starting CAMRESE after Childbirth

Do not start until 4 weeks after delivery, due to the increased risk of thromboembolic disease. Start contraceptive therapy with CAMRESE following the instructions for women not currently using hormonal contraception. Use additional non-hormonal contraception (such as condoms and spermicide) until the patient has taken a light blue-green tablet for 7 consecutive days [see Contraindications (4) and Warnings and Precautions (5.1)].

If the woman has not yet had a period postpartum, consider the possibility of ovulation and conception occurring prior to use of CAMRESE [see Warnings and Precautions (5.1), Use in Specific Populations (8.1)].

2.2 Dosing CAMRESE

Take one tablet by mouth at the same time every day. The dosage of CAMRESE is one light blue-green tablet daily for 84 consecutive days, followed by one yellow tablet daily for 7 days. To achieve maximum contraceptive effectiveness, CAMRESE must be taken exactly as directed, in the order directed, and at intervals not exceeding 24 hours. The failure rate may increase when pills are missed or taken incorrectly.

2.3 Missed Doses

Table 1. Instructions for Missed CAMRESE Tablets

If one light blue-green tablet is missed | Take the missed tablet as soon as possible. Take the next tablet at the regular time. Continue taking one tablet a day until the pack is finished. A backup birth control method is not required if the patient has sex.
If two light blue-green tablet in a row are missed | Take the two missed tablets as soon as possible, and the next two tablets the next day. Continue taking one tablet a day until the pack is finished. Use additional nonhormonal contraception (such as condoms and spermicide) until tablets have been taken for 7 days after missing tablets.
If three or more light blue-green pills in a row are missed | Throw away the missed pills. Continue taking one tablet every day as indicated on the pack until the pack is finished. Bleeding may occur during the week following the missed tablets. Use additional nonhormonal contraception (such as condoms and spermicide) until tablets have been taken for 7 days after missing tablets.
If any of the seven yellow tablets are missed | Throw away the missed tablets. Continue taking the remaining tablets until the pack is finished. A backup birth control method is not needed.

2.4 Advice in Case of Gastrointestinal Disturbances

In case of prolonged vomiting or diarrhea, absorption may not be complete and additional contraceptive measures should be taken.

3 DOSAGE FORMS AND STRENGTHS

CAMRESE tablets (levonorgestrel/ethinyl estradiol tablets and ethinyl estradiol tablets) are available in Extended-Cycle Tablet Dispensers, each containing a 13-week supply of tablets: 84 light blue-green tablets, each containing 0.15 mg of levonorgestrel and 0.03 mg ethinyl estradiol, and 7 yellow tablets each containing 0.01 mg of ethinyl estradiol. The light blue-green tablets are round, film-coated, biconvex, unscored tablets debossed with stylized b on one side and 555 on the other side. The yellow tablets are round, biconvex, film-coated, unscored tablets debossed with stylized b on one side and 556 on the other side.

4 CONTRAINDICATIONS

CAMRESE is contraindicated in females who are known to have or develop the following conditions:

- A high risk of arterial or venous thrombotic diseases. Examples include females who are known to:
  - Smoke, if over age 35 [see Boxed Warning and Warnings and Precautions (5.1)].
  - Have current or history of deep vein thrombosis or pulmonary embolism [see Warnings and Precautions (5.1)].
  - Have cerebrovascular disease [see Warnings and Precautions (5.1)]
  - Have coronary artery disease [see Warnings and Precautions (5.1)].
  - Have thrombogenic valvular or thrombogenic rhythm diseases of the heart (for example, subacute bacterial endocarditis with valvular disease, or atrial fibrillation) [see Warnings and Precautions (5.1)].
  - Have inherited or acquired hypercoagulopathies [see Warnings and Precautions (5.1)].
  - Have uncontrolled hypertension or hypertension with vascular disease [see Warnings and Precautions (5.3)].
  - Have diabetes mellitus and are over age 35, diabetes mellitus with hypertension or with vascular disease or other end-organ damage, or diabetes mellitus of > 20 years duration [see Warnings and Precautions (5.7)].
  - Have headaches with focal neurological symptoms, migraine headaches with aura, or over age 35 with any migraine headaches [see Warnings and Precautions (5.8)].

- Current diagnosis of, or history of, breast cancer, which may be hormone sensitive [see Warnings and Precautions (5.11)].
- Liver tumors, acute viral hepatitis, or severe (decompensated) cirrhosis [see Warnings and Precautions (5.2) and Use in Specific Populations (8.6)].
- Undiagnosed abnormal uterine bleeding [see Warnings and Precautions (5.9)].
- Use of Hepatitis C drug combinations containing ombitasvir/paritaprevir/ritonavir, with or without dasabuvir, due to the potential for ALT elevations [see Warnings and Precautions (5.4)].

5 WARNINGS AND PRECAUTIONS

5.1 Thromboembolic Disorders and Other Vascular Conditions

- Stop CAMRESE if an arterial or deep venous thrombotic/thromboembolic event occurs.
- Stop CAMRESE if there is unexplained loss of vision, proptosis, diplopia, papilledema, or retinal vascular lesions and evaluate for retinal vein thrombosis immediately.
- Discontinue CAMRESE during prolonged immobilization. If feasible, stop CAMRESE at least 4 weeks before and through 2 weeks after major surgery, or other surgeries known to have an elevated risk of thromboembolism.
- Start CAMRESE no earlier than 4 weeks after delivery, in women who are not breastfeeding. The risk of postpartum thromboembolism decreases after the third postpartum week, whereas the risk of ovulation increases after the third postpartum week.
- Before starting CAMRESE evaluate any past medical history or family history of thrombotic or thromboembolic disorders and consider whether the history suggests an inherited or acquired hypercoagulopathy. CAMRESE is contraindicated in women with a high risk of arterial or venous/thromboembolic diseases [see Contraindications (4)].

Arterial Events

COCs increase the risk of cardiovascular events and cerebrovascular events, such as myocardial infarction and stroke. The risk is greater among older women (> 35 years of age), smokers, and females with hypertension, dyslipidemia, diabetes, or obesity.

CAMRESE is contraindicated in women over 35 years of age who smoke [see Contraindications (4)]. Cigarette smoking increases the risk of serious cardiovascular events from COC use. This risk increases with age, particularly in women over 35 years of age, and with the number of cigarettes smoked.

Venous Events

Use of COCs increases the risk of venous thromboembolic events (VTEs), such as deep vein thrombosis and pulmonary embolism. Risk factors for VTEs include smoking, obesity, and family history of VTE, in addition to other factors that contraindicate use of CHCs [see Contraindications (4)]. While the increased risk of VTE associated with use of COCs is well-established, the rates of VTE are even greater during pregnancy, and especially during the postpartum period (see Figure 1). The rate of VTE in females using COCs has been estimated to be 3 to 9 cases per 10,000 woman years.

The risk of VTE is highest during the first year of use of a COC and when restarting hormonal contraception after a break of four weeks or longer. The risk of thromboembolic disease due to COCs gradually disappears after COC use is discontinued.

Figure 1 shows the risk of developing a VTE for women who are not pregnant and do not use oral contraceptives, for women who use oral contraceptives, and for women in the postpartum period. To put the risk of developing a VTE into perspective: If 10,000 women who are not pregnant and do not use oral contraceptives are followed for one year, between 1 and 5 of these women will develop a VTE.

Use of CAMRESE provides women with more hormonal exposure on a yearly basis than conventional monthly oral contraceptives containing the same strength synthetic estrogens and progestins (an additional 9 and 13 weeks of exposure to progestin and estrogen, respectively, per year).

5.2 Liver Disease

Elevated Liver Enzymes

CAMRESE is contraindicated in women with acute viral hepatitis or severe (decompensated) cirrhosis of the liver [see Contraindications (4)]. Acute liver test abnormalities may necessitate the discontinuation of CAMRESE until the liver tests return to normal and CAMRESE causation has been excluded. Discontinue CAMRESE if jaundice develops.

Liver Tumors

CAMRESE is contraindicated in women with benign or malignant liver tumors [see Contraindications (4)]. COCs increase the risk of hepatic adenomas. An estimate of the attributable risk is 3.3 cases/100,000 COC users. Rupture of hepatic adenomas may cause death from abdominal hemorrhage.

Studies have shown an increased risk of developing hepatocellular carcinoma in long-term (> 8 years) COC users. The attributable risk of liver cancers in COC users is less than one case per million users.

5.3 Hypertension

CAMRESE is contraindicated in women with uncontrolled hypertension or hypertension with vascular disease [see Contraindications (4)]. For all women, including those with well-controlled hypertension, monitor blood pressure at routine visits and stop CAMRESE if blood pressure rises significantly.

An increase in blood pressure has been reported in women taking COCs, and this increase is more likely in older women and with extended duration of use. The effect of COCs on blood pressure may vary according to the progestin in the COC.

5.4 Risk of Liver Enzyme Elevations with Concomitant Hepatitis C Treatment

During clinical trials with the Hepatitis C combination drug regimen that contains ombitasvir/paritaprevir/ritonavir, with or without dasabuvir, ALT elevations greater than 5 times the upper limit of normal (ULN), including some cases greater than 20 times the ULN, were significantly more frequent in women using ethinyl estradiol-containing medications, such as CAMRESE. Discontinue CAMRESE prior to starting therapy with the combination drug regimen ombitasvir/paritaprevir/ritonavir, with or without dasabuvir [see Contraindications (4)]. CAMRESE can be restarted approximately 2 weeks following completion of treatment with the Hepatitis C combination drug regimen.

5.5 Age-related Considerations

The risk for cardiovascular disease and prevalence of risk factors for cardiovascular disease increases with age. Certain conditions, such as smoking and migraine headache without aura, that do not contraindicate COC use in younger females, are contraindications to use in women over 35 years of age [see Contraindications (4) and Warnings and Precautions (5.1)]. Consider the presence of underlying risk factors that may increase the risk of cardiovascular disease or VTE, particularly before initiating a COC for women over 35 years, such as:

- Hypertension
- Diabetes
- Dyslipidemia
- Obesity

5.6 Gallbladder Disease

Studies suggest a small increased relative risk of developing gallbladder disease among COC users. Use of COCs, including CAMRESE, may also worsen existing gallbladder disease.

A past history of COC-related cholestasis predicts an increased risk with subsequent COC use. Females with a history of pregnancy-related cholestasis may be at an increased risk for COC-related cholestasis.

5.7 Adverse Carbohydrate and Lipid Metabolic Effects

Hyperglycemia

CAMRESE is contraindicated in diabetic women over age 35, or females who have diabetes with hypertension, nephropathy, retinopathy, neuropathy, other vascular disease, or females with diabetes of > 20 years duration [see Contraindications (4)]. CAMRESE may decrease glucose tolerance. Carefully monitor prediabetic and diabetic women who are taking CAMRESE.

Dyslipidemia

Consider alternative contraception for women with uncontrolled dyslipidemia. CAMRESE may cause adverse lipid changes.

Women with hypertriglyceridemia, or a family history thereof, may have an increase in serum triglyceride concentrations when using CAMRESE, which may increase the risk of pancreatitis.

5.8 Headache

CAMRESE is contraindicated in females who have headaches with focal neurological symptoms or have migraine headaches with aura, and in women over 35 years of age who have migraine headaches with or without aura [see Contraindications (4)].

If a woman taking CAMRESE develops new headaches that are recurrent, persistent, or severe, evaluate the cause and discontinue CAMRESE if indicated. Consider discontinuation of CAMRESE if there is an increased frequency or severity of migraine during COC use (which may be prodromal of a cerebrovascular event).

5.9 Bleeding Irregularities and Amenorrhea

Unscheduled Bleeding and Spotting

Women using CAMRESE may experience unscheduled (breakthrough or intracyclic) bleeding and spotting, especially during the first 3 months of use. Bleeding irregularities may resolve over time or by changing to a different contraceptive product. If unscheduled bleeding persists or occurs after previously regular cycles, evaluate for causes such as pregnancy or malignancy.

When prescribing CAMRESE, the occurrence of fewer planned menses (4 per year instead of 13 per year) should be weighed against the occurrence of increased unscheduled bleeding and/or spotting. The primary clinical trial (PSE-301) that evaluated the efficacy of CAMRESE also assessed unscheduled bleeding. The participants in the 12-month clinical trial (N=1,006) completed the equivalent of 8,681 28-day cycles of exposure and were composed primarily of women who had used oral contraceptives previously (89%) as opposed to new users (11%). A total of 82 (8.2%) of the women discontinued CAMRESE, at least in part, due to bleeding or spotting.

Scheduled (withdrawal) bleeding and/or spotting remained fairly constant over time, with an average of 3 days of bleeding and/or spotting per each 91-day cycle. Unscheduled bleeding and unscheduled spotting decreased over successive 91-day cycles. Table 1 below presents the number of days with unscheduled bleeding in treatment cycles 1 and 4. Table 2 presents the number of days with unscheduled spotting in treatment cycles 1 and 4.

Table 2: Total Number of Days with Unscheduled Bleeding

91-Day Treatment Cycle | Days per 84-Day Interval |  |  |  | Days per 28-Day Interval
91-Day Treatment Cycle | Q1 | Median | Q3 | Mean | Mean
1st | 1 | 4 | 10 | 6.9 | 1.7
4th | 0 | 1 | 4 | 3.2 | 0.8

Q1=Quartile 1: 25% of women had this number of days of unscheduled bleeding

Median: 50% of women had ≤ this number of days of unscheduled bleeding

Q3=Quartile 3: 75% of women had ≤ this number of days of unscheduled bleeding

Table 3: Total Number of Days with Unscheduled Spotting

91-Day Treatment Cycle | Days per 84-Day Interval |  |  |  | Days per 28-Day Interval
91-Day Treatment Cycle | Q1 | Median | Q3 | Mean | Mean
1st | 1 | 4 | 11 | 7.4 | 1.9
4th | 0 | 2 | 7 | 4.4 | 1.1

Q1=Quartile 1: 25% of women had ≤ this number of days of unscheduled spotting

Median: 50% of women had ≤ this number of days of unscheduled spotting

Q3=Quartile 3: 75% of women had ≤ this number of days of unscheduled spotting

Figure 2 shows the percentage of CAMRESE subjects participating in trial PSE-301 with ≥ 7 days or ≥ 20 days of unscheduled bleeding and/or spotting, or only unscheduled bleeding, during each 91-day treatment cycle.

Figure 2: Percent of Women Taking CAMRESE who Reported Unscheduled Bleeding and/or Spotting or only Unscheduled Bleeding

If unscheduled spotting or bleeding occurs, instruct the patient to continue on the same regimen. If the bleeding is persistent or prolonged, advise the patient to consult her healthcare provider.

Amenorrhea and Oligomenorrhea

Women who use CAMRESE may experience absence of scheduled (withdrawal) bleeding, even if they are not pregnant.

If scheduled bleeding does not occur, consider the possibility of pregnancy.

After discontinuation of CAMRESE, amenorrhea or oligomenorrhea may occur, especially if these conditions were pre-existent.

5.10 Depression

Carefully observe women with a history of depression and discontinue CAMRESE if depression recurs to a serious degree. Data on the association of COCs with the onset of depression or exacerbation of existing depression are limited.

5.11 Malignant Neoplasms

Breast Cancer

CAMRESE is contraindicated in females who currently have or have had breast cancer because breast cancer may be hormonally sensitive [see Contraindications (4)].

Epidemiology studies have not found a consistent association between use of combined oral contraceptives (COCs) and breast cancer risk. Studies do not show an association between ever (current or past) use of COCs and risk of breast cancer. However, some studies report a small increase in the risk of breast cancer among current or recent users (<6 months since last use) and current users with longer duration of COC use [see Postmarketing Experience (6.2)].

Cervical Cancer

Some studies suggest that COCs are associated with an increase in the risk of cervical cancer or intraepithelial neoplasia. However, there is controversy about the extent to which these findings are due to differences in sexual behavior and other factors.

5.12 Effect on Binding Globulins

The estrogen component of CAMRESE may raise the serum concentrations of thyroxine-binding globulin, sex hormone-binding globulin, and cortisol-binding globulin. The dose of replacement thyroid hormone or cortisol therapy may need to be increased.

5.13 Hereditary Angioedema

In females with hereditary angioedema, exogenous estrogens, including CAMRESE, may induce or exacerbate symptoms of hereditary angioedema.

5.14 Chloasma

Chloasma may occur with CAMRESE use, especially in women with a history of chloasma gravidarum. Advise women with a history of chloasma to avoid exposure to the sun or ultraviolet radiation while using CAMRESE.

6 ADVERSE REACTIONS

The following serious adverse reactions with the use of COCs are discussed elsewhere in the labeling:

- Serious cardiovascular events and stroke [see Boxed Warning and Warnings and Precautions (5.1)]
- Vascular events [see Warnings and Precautions (5.1)]
- Liver disease [see Warnings and Precautions (5.2)]

6.1 Clinical Trial Experience

Because clinical trials are conducted under widely varying conditions, adverse reaction rates observed in the clinical trials of a drug cannot be directly compared to the rates in the clinical trials of another drug and may not reflect the rates observed in practice.

The clinical trial that evaluated the safety and efficacy of CAMRESE was a 12-month, randomized, multicenter, open-label study, which enrolled women aged 18-40, of whom 1,006 took at least one dose of CAMRESE.

Adverse Reactions Leading to Study Discontinuation: 16.3% of the women discontinued from the clinical trial due to an adverse reaction; the most common adverse reactions (≥ 1% of women) leading to discontinuation were irregular and/or heavy uterine bleeding (5.9%), weight gain (2.4%), mood changes (1.5%), and acne (1.0%).

Common Treatment-Emergent Adverse Reactions (≥ 5% of women): irregular and/or heavy uterine bleeding (17%), weight gain (5%), acne (5%).

Serious Adverse Reactions: migraine, cholecystitis, cholelithiasis, pancreatitis, abdominal pain, and major depressive disorder.

6.2 Postmarketing Experience

Five studies that compared breast cancer risk between ever-users (current or past use) of COCs and never-users of COCs reported no association between ever use of COCs and breast cancer risk, with effect estimates ranging from 0.90 - 1.12 (Figure 3).

Three studies compared breast cancer risk between current or recent COC users (<6 months since last use) and never users of COCs (Figure 3). One of these studies reported no association between breast cancer risk and COC use. The other two studies found an increased relative risk of 1.19 - 1.33 with current or recent use. Both of these studies found an increased risk of breast cancer with current use of longer duration, with relative risks ranging from 1.03 with less than one year of COC use to approximately 1.4 with more than 8-10 years of COC use.

Figure 3: Relevant Studies of Risk of Breast Cancer with Combined Oral Contraceptives

RR = relative risk; OR = odds ratio; HR = hazard ratio. “ever COC” are females with current or past COC use; “never COC use” are females that never used COCs.

The following adverse reactions have been identified during post-approval use of CAMRESE. Because these reactions are reported voluntarily from a population of uncertain size, it is not possible to reliably estimate their frequency of establish a causal relationship to drug exposure.

Gastrointestinal disorders: abdominal distension, vomiting

General disorders and administration site conditions: chest pain, fatigue, malaise, edema peripheral, pain

Immune system disorders: hypersensitivity reaction

Investigations: blood pressure increased

Musculoskeletal and connective tissue disorders: muscle spasms, pain in extremity

Nervous system disorders: dizziness, loss of consciousness

Psychiatric disorders: insomnia

Reproductive and breast disorders: dysmenorrhea

Respiratory, thoracic and mediastinal disorders: pulmonary embolism, pulmonary thrombosis

Skin and subcutaneous tissue disorders: alopecia

Vascular disorders: thrombosis

7 DRUG INTERACTIONS

The sections below provide information on substances for which data on drug interactions with COCs are available. There is little information available about the clinical effect of most drug interactions that may affect COCs. However, based on the known pharmacokinetic effects of these drugs, clinical strategies to minimize any potential adverse effect on contraceptive effectiveness or safety are suggested.

Consult the approved product labeling of all concurrently used drugs to obtain further information about interactions with COCs or the potential for metabolic enzyme or transporter system alterations.

No drug-drug interaction studies were conducted with CAMRESE.

7.1 Effects of Other Drugs on Combined Oral Contraceptives

Substances Decreasing the Plasma Concentrations of COCs and Potentially Diminishing the Efficacy of COCs:

Table 4 includes substances that demonstrated an important drug interaction with CAMRESE.

Table 4: Significant Drug Interactions Involving Substances That Affect COCs

Metabolic Enzyme Inducers
Clinical effect | - Concomitant use of COCs with metabolic enzyme inducers may decrease the plasma concentrations of the estrogen and/or progestin component of COCs. - Decreased exposure of the estrogen and/or progestin component of COCs may potentially diminish the effectiveness of COCs and may lead to contraceptive failure or an increase in breakthrough bleeding.
Prevention or management | - Counsel females to use an alternative method of contraception or a backup method when enzyme inducers are used with COCs. - Continue backup contraception for 28 days after discontinuing the enzyme inducer to maintain contraceptive reliability.
Examples | Aprepitant, barbiturates, bosentan, carbamazepine, efavirenz, felbamate, griseofulvin, oxcarbazepine, phenytoin, rifampin, rifabutin, rufinamide, topiramate, products containing St. John’s worta, and certain protease inhibitors (see separate section on protease inhibitors below).
Colesevelam
Clinical effect | - Concomitant use of COCs with colesevelam significantly decreases systemic exposure of ethinyl estradiol. - Decreased exposure of the estrogen component of COCs may potentially reduce contraceptive efficacy or result in an increase in breakthrough bleeding, depending on the strength of ethinyl estradiol in the CHC.
Prevention or management | Administer 4 or more hours apart to attenuate this drug interaction.

a Induction potency of St. John’s wort may vary widely based on preparation.

Substances increasing the systemic exposure of COCs:

Co-administration of atorvastatin or rosuvastatin and COCs containing ethinyl estradiol increase systemic exposure of ethinyl estradiol by approximately 20 to 25 percent. Ascorbic acid and acetaminophen may increase systemic exposure of ethinyl estradiol, possibly by inhibition of conjugation. CYP3A inhibitors such as itraconazole, voriconazole, fluconazole, grapefruit juice, or ketoconazole may increase systemic exposure of the estrogen and/or progestin component of COCs.

Human immunodeficiency virus (HIV)/hepatitis C virus (HCV) protease inhibitors and non-nucleoside reverse transcriptase inhibitors:

Significant decreases in systemic exposure of the estrogen and/or progestin have been noted when COCs are co-administered with some HIV protease inhibitors (e.g., nelfinavir, ritonavir, darunavir/ritonavir, (fos)amprenavir/ritonavir, lopinavir/ritonavir, and tipranavir/ritonavir), some HCV protease inhibitors (e.g., boceprevir and telaprevir), and some non-nucleoside reverse transcriptase inhibitors (e.g., nevirapine).

In contrast, significant increases in systemic exposure of the estrogen and/or progestin have been noted when COCs are co-administered with certain other HIV protease inhibitors (e.g., indinavir and atazanavir/ritonavir) and with other non-nucleoside reverse transcriptase inhibitors (e.g., etravirine).

7.2 Effects of Combined Oral Contraceptives on Other Drugs

Table 5 provides significant drug interaction information for drugs co-administered with CAMRESE.

Table 5: Significant Drug Interaction Information for Drugs Co-Administered With COCs

Lamotrigine
Clinical effect | - Concomitant use of COCs with lamotrigine may significantly decrease systemic exposure of lamotrigine due to induction of lamotrigine glucuronidation. - Decreased systemic exposure of lamotrigine may reduce seizure control.
Prevention or management | Dose adjustment may be necessary. Consult the approved product labeling for lamotrigine.
Thyroid Hormone Replacement Therapy or Corticosteroid Replacement Therapy
Clinical effect | Concomitant use of COCs with thyroid hormone replacement therapy or corticosteroid replacement therapy may increase systemic exposure of thyroid-binding and cortisol-binding globulin [see Warnings and Precautions (5.12)].
Prevention or management | The dose of replacement thyroid hormone or cortisol therapy may need to be increased. Consult the approved product labeling for the therapy in use [see Warnings and Precautions (5.12)].
Other Drugs
Clinical effect | Concomitant use of COCs may decrease systemic exposure of acetaminophen, morphine, salicylic acid, and temazepam. Concomitant use with ethinyl estradiol-containing COCs may increase systemic exposure of other drugs (e.g., cyclosporine, prednisolone, theophylline, tizanidine, and voriconazole).
Prevention or management | The dosage of drugs that can be affected by this interaction may need to be increased. Consult the approved product labeling for the concomitantly used drug.

7.3 Concomitant Use with Hepatitis C Virus (HCV) Combination Therapy – Liver Enzyme Elevation

Co-administration of CAMRESE with HCV drug combinations containing ombitasvir/paritaprevir/ritonavir, with or without dasabuvir is contraindicated due to potential for ALT elevations [see Warnings and Precautions (5.4)]. Co-administration of CAMRESE and glecaprevir/pibrentasvir is not recommended due to potential for ALT elevations.

7.4 Effect on Laboratory Tests

The use of COCs may influence the results of certain laboratory tests, such as coagulation factors, lipids, glucose tolerance, and binding proteins.

8 USE IN SPECIFIC POPULATIONS

8.1 Pregnancy

Risk Summary

There is no use for contraception in pregnancy; therefore, CAMRESE should be discontinued during pregnancy. Epidemiologic studies and meta-analyses have not found an increased risk of genital or non-genital birth defects (including cardiac anomalies and limb-reduction defects) following exposure to COCs before conception or during early pregnancy.

In the U.S. general population, the estimated background risk of major birth defects and miscarriage in clinically recognized pregnancies is 2 to 4 percent and 15 to 20 percent, respectively.

8.2 Lactation

Risk Summary

Contraceptive hormones and/or metabolites are present in human milk. COCs can reduce milk production in breastfeeding females. This reduction can occur at any time but is less likely to occur once breastfeeding is well-established. When possible, advise the nursing woman to use other methods of contraception until she discontinues breastfeeding [See Dosage and Administration (2.1]. The developmental and health benefits of breastfeeding should be considered along with the mother’s clinical need for CAMRESE and any potential adverse effects on the breastfed child from CAMRESE or the underlying maternal condition.

8.4 Pediatric Use

Safety and efficacy of CAMRESE have been established in women of reproductive age. Safety and efficacy are expected to be the same for postpubertal adolescents under the age of 18 as for users 18 years and older. Use of CAMRESE before menarche is not indicated.

8.5 Geriatric Use

CAMRESE has not been studied in postmenopausal women and is not indicated in this population.

8.6 Hepatic Impairment

No studies have been conducted to evaluate the effect of hepatic disease on the disposition of CAMRESE. However, steroid hormones may be poorly metabolized in patients with impaired liver function. CAMRESE is contraindicated in females with acute hepatitis or severe decompensated cirrhosis [see Contraindications (4) and Warnings and Precautions (5.2)].

10 OVERDOSAGE

There have been no reports of serious ill effects from overdose of oral contraceptives, including ingestion by children. Overdosage may cause uterine bleeding in females and nausea.

11 DESCRIPTION

CAMRESE (levonorgestrel/ethinyl estradiol tablets and ethinyl estradiol tablets) is an extended-cycle oral contraceptive consisting of 84 light blue-green tablets each containing 0.15 mg of levonorgestrel, a synthetic progestogen and 0.03 mg of ethinyl estradiol, and 7 yellow tablets containing 0.01 mg of ethinyl estradiol.

The structural formulas for the active components are:

Levonorgestrel

C21H28O2 MW: 312.4

Levonorgestrel is chemically 18,19-Dinorpregn-4-en-20-yn-3-one, 13-ethyl-17-hydroxy-, (17α)-, (-)-.

Ethinyl Estradiol

C20H24O2 MW: 296.4

Ethinyl Estradiol is 19-Norpregna-1,3,5(10)-trien-20-yne-3,17-diol, (17α)-.

Each light blue-green tablet contains the following inactive ingredients: anhydrous lactose, D&C yellow no. 10 aluminum lake, FD&C blue no. 1 aluminum lake, FD&C yellow no. 6/Sunset yellow aluminum lake, hypromellose, lactose monohydrate, magnesium stearate, microcrystalline cellulose, titanium dioxide and triacetin.

Each yellow tablet contains the following inactive ingredients: anhydrous lactose, D&C yellow no. 10 aluminum lake, FD&C yellow no. 6/Sunset yellow aluminum lake, hypromellose, magnesium stearate, microcrystalline cellulose, polacrilin potassium, polyethylene glycol, polysorbate 80 and titanium dioxide.

12 CLINICAL PHARMACOLOGY

12.1 Mechanism of Action

COCs prevent pregnancy primarily by suppressing ovulation.

12.3 Pharmacokinetics

Absorption

Ethinyl estradiol and levonorgestrel are absorbed with maximum plasma concentrations occurring within 2 hours after CAMRESE administration. Levonorgestrel is completely absorbed after oral administration (bioavailability nearly 100%) and is not subject to first-pass metabolism. Ethinyl estradiol is absorbed from the gastrointestinal tract but, due to first-pass metabolism in gut mucosa and liver, the bioavailability of ethinyl estradiol is approximately 43%.

The daily exposure to levonorgestrel and ethinyl estradiol on Day 21, corresponding to the end of a typical 3-week contraceptive regimen, and on Day 84, at the end of an extended cycle regimen, were similar. There was no additional accumulation of ethinyl estradiol after dosing a 0.03 mg ethinyl estradiol tablet during Days 84-91. The mean plasma pharmacokinetic parameters of CAMRESE following a single dose of one levonorgestrel/ethinyl estradiol combination tablet, for 84 days, in normal healthy women are reported in Table 6.

Table 6: Mean Pharmacokinetic Parameters for CAMRESE during Daily One Tablet Dosing for 84 Days

 | AUC0-24 hr (mean ± SD) | Cmax; (mean ± SD) | Tmax; (mean ± SD)
 | Levonorgestrel
Day 1 | 18.2 ± 6.1 ng•hr/mL | 3.0 ± 1.0 ng/mL | 1.3 ± 0.4 hours
Day 21 | 64.4 ± 25.1 ng•hr/mL | 6.2 ± 1.6 ng/mL | 1.3 ± 0.4 hours
Day 84 | 60.2 ± 24.6 ng•hr/mL | 5.5 ± 1.6 ng/mL | 1.3 ± 0.3 hours
 | Ethinyl Estradiol
Day 1 | 509.3 ± 172.0 pg•hr/mL | 69.8 ± 26 pg/mL | 1.5 ± 0.3 hours
Day 21 | 837.1 ± 271.2 pg•hr/mL | 99.6 ± 31 pg/mL | 1.5 ± 0.3 hours
Day 84 | 791.5 ± 215.0 pg•hr/mL | 91.3 ± 32 pg/mL | 1.6 ± 0.3 hours

The effect of food on the rate and the extent of levonorgestrel and ethinyl estradiol absorption following oral administration of CAMRESE has not been evaluated.

Distribution

The apparent volume of distribution of levonorgestrel and ethinyl estradiol are reported to be approximately 1.8 L/kg and 4.3 L/kg, respectively. Levonorgestrel is about 97.5 - 99% protein-bound, principally to sex hormone binding globulin (SHBG) and, to a lesser extent, serum albumin. Ethinyl estradiol is about 95 - 97% bound to serum albumin. Ethinyl estradiol does not bind to SHBG, but induces SHBG synthesis, which leads to decreased levonorgestrel clearance. Following repeated daily dosing of levonorgestrel/ethinyl estradiol oral contraceptives, levonorgestrel plasma concentrations accumulate more than predicted based on single-dose pharmacokinetics, due in part, to increased SHBG levels that are induced by ethinyl estradiol, and a possible reduction in hepatic metabolic capacity.

Metabolism

Following absorption, levonorgestrel is conjugated at the 17β-OH position to form sulfate and to a lesser extent, glucuronide conjugates in plasma. Significant amounts of conjugated and unconjugated 3α,5β-tetrahydrolevonorgestrel are also present in plasma, along with much smaller amounts of 3α,5α-tetrahydrolevonorgestrel and 16β-hydroxylevonorgestrel. Levonorgestrel and its phase I metabolites are excreted primarily as glucuronide conjugates. Metabolic clearance rates may differ among individuals by several-fold, and this may account in part for the wide variation observed in levonorgestrel concentrations among users.

First-pass metabolism of ethinyl estradiol involves formation of ethinyl estradiol-3-sulfate in the gut wall, followed by 2-hydroxylation of a portion of the remaining untransformed ethinyl estradiol by hepatic cytochrome P-450 3A4 (CYP3A4). Levels of CYP3A4 vary widely among individuals and can explain the variation in rates of ethinyl estradiol hydroxylation. Hydroxylation at the 4-, 6-, and 16- positions may also occur, although to a much lesser extent than 2-hydroxylation. The various hydroxylated metabolites are subject to further methylation and/or conjugation.

Excretion

About 45% of levonorgestrel and its metabolites are excreted in the urine and about 32% are excreted in feces, mostly as glucuronide conjugates. The terminal elimination half-life for levonorgestrel after a single dose of CAMRESE was about 34 hours.

Ethinyl estradiol is excreted in the urine and feces as glucuronide and sulfate conjugates, and it undergoes enterohepatic recirculation. The terminal elimination half-life of ethinyl estradiol after a single dose of CAMRESE was found to be about 18 hours.

Race

The effect of race on the pharmacokinetics of CAMRESE has not been evaluated.

13 NONCLINICAL TOXICOLOGY

13.1 Carcinogenesis, Mutagenesis, Impairment of Fertility

[See Warnings and Precautions (5.2, 5.11)].

14 CLINICAL STUDIES

In a 12-month, multicenter, randomized, open-label clinical trial, 1,006 women aged 18-40 were studied to assess the safety and efficacy of CAMRESE, completing the equivalent of 8,681 28-day cycles of exposure. The racial demographic of those enrolled was: Caucasian (80%), African-American (11%), Hispanic (5%), Asian (2%), and Other (2%). There were no exclusions for body mass index (BMI) or weight. The weight range of those women treated was 91 to 360 lbs., with a mean weight of 156 lbs. Among the women in the trial, 63% were current or recent hormonal contraceptive users, 26% were prior users (who had used hormonal contraceptives in the past but not in the 6 months prior to enrollment), and 11% were new starts. Of treated women, 14.8% were lost to follow-up, 16.3% discontinued due to an adverse event, and 12.9% discontinued by withdrawing their consent.

The pregnancy rate (Pearl Index [PI]) in women aged 18-35 years was 1.34 pregnancies per 100 women-years of use (95% confidence interval 0.54-2.75), based on 7 pregnancies that occurred after the onset of treatment and within 14 days after the last combination pill. Cycles in which conception did not occur, but which included the use of backup contraception, were not included in the calculation of the PI. The PI includes patients who did not take the drug correctly.

16 HOW SUPPLIED/STORAGE AND HANDLING

How Supplied

CAMRESE tablets (levonorgestrel/ethinyl estradiol tablets and ethinyl estradiol tablets) are available in Extended-Cycle Tablet Dispensers (NDC 0093-3134-82), each containing a 13-week supply of tablets: 84 light blue-green tablets, each containing 0.15 mg of levonorgestrel and 0.03 mg ethinyl estradiol, and 7 yellow tablets each containing 0.01 mg of ethinyl estradiol. The light blue-green tablets are round, film-coated, biconvex, unscored tablets debossed with stylized b on one side and 555 on the other side. The yellow tablets are round, biconvex, film-coated, unscored tablets debossed with stylized b on one side and 556 on the other side.

Box of 2 Extended-Cycle Tablet Dispensers NDC 0093-3134-82

Storage and Handling

Store at 20°C to 25°C (68°F to 77° F); excursions permitted to 15ºC to 30ºC (59ºF to 86ºF) [See USP Controlled Room Temperature].

17 PATIENT COUNSELING INFORMATION

Advise the patient to read the FDA-approved Patient Labeling (Patient Information and Instructions for Use).

Counsel patients about the following information:

Cigarette Smoking

Cigarette smoking increases the risk of serious cardiovascular events from COC use. Women who are over 35 years old and smoke should not use CAMRESE [see Boxed Warning and Warnings and Precautions (5.1)].

Venous Thromboembolism

Increased risk of VTE compared to non-users of COCs is greatest after initially starting a COC or restarting (following a 4-week or greater interruption in intake) the same or a different COC [see Warnings and Precautions (5.1)].

Use during Pregnancy

Instruct females to stop further intake of CAMRESE if pregnancy is confirmed during treatment.

Sexually Transmitted Infections

CAMRESE does not protect against HIV-infection (AIDS) and other sexually transmitted infections.

Dosing and Missed Pill Instructions

Patients should take one tablet daily by mouth at the same time every day.

Instruct patients what to do in the event pills are missed. See, “What to do if you miss pills” section of FDA-Approved Instructions for Use [see Dosage and Administration (2.3)].

Need for Additional Contraception

Postpartum females who have not yet had a period when they start CAMRESE need to use an additional method of contraception until they have taken a light blue-green tablet for 7 consecutive days [see Dosage and Administration (2.1)].

There is a need to use a backup or alternative method of contraception when enzyme inducers are used with CAMRESE [see Drug Interactions (7.1)].

Lactation

CAMRESE may reduce breast milk production. This is less likely to occur if breastfeeding is well established. When possible, nursing women should use other methods of contraception until they have discontinued breastfeeding [see Use in Specific Populations (8.2)].

Amenorrhea and Possible Symptoms of Pregnancy

Amenorrhea may occur. Advise patients to contact a healthcare provider in the event of amenorrhea with symptoms of pregnancy, such as morning sickness or unusual breast tenderness [see Warnings and Precautions (5.9)].

Fertility Following Discontinuation of CAMRESE

Resumption of pre-treatment ovarian function is expected, generally within 8 weeks after discontinuation of CAMRESE.

Depression

Depressed mood and depression may occur. Women should contact their healthcare provider if mood changes and depressive symptoms occur, including shortly after initiating the treatment [see Warnings and Precautions (5.10)].

Manufactured for:
Teva Pharmaceuticals
Parsippany, NJ 07054

CAMPI-003

Rev. 10/2024

© 2024 Teva Pharmaceuticals, Inc.

FDA-Approved Patient Labeling

PATIENT INFORMATION

CAMRESE®

(levonorgestrel/ethinyl estradiol and ethinyl estradiol)

WARNING TO WOMEN WHO SMOKE

Do not use CAMRESE if you smoke cigarettes and are over 35 years old. Smoking increases your risk of serious cardiovascular side effects from birth control pills, including death from heart attack, blood clots or stroke. This risk increases with age and the number of cigarettes you smoke.

What is the most important information I should know about CAMRESE?

Do not use CAMRESE if you smoke cigarettes and are over 35 years old. Smoking increases your risk of serious cardiovascular side effects from birth control pills, including death from heart attack, blood clots or stroke. This risk increases with age and the number of cigarettes you smoke.

What is CAMRESE?

CAMRESE is a birth control pill (hormonal contraceptive) used by women to prevent pregnancy. It contains two female hormones, an estrogen called ethinyl estradiol, and a progestin called levonorgestrel.

CAMRESE does not protect against HIV infection (AIDS) and other sexually transmitted infections.

How Does CAMRESE Work for contraception?

Your chance of getting pregnant depends on how well you follow the directions for taking your birth control pills. The more carefully you follow the directions, the less chance you have of getting pregnant.

Based on the results of a single clinical study lasting 12 months, 1 to 3 women, out of 100 women, may get pregnant during the first year they use CAMRESE.

The following chart shows the chance of getting pregnant for women who use different methods of birth control. Each box on the chart contains a list of birth control methods that are similar in effectiveness. The most effective methods are at the top of the chart. The box on the bottom of the chart shows the chance of getting pregnant for women who do not use birth control and are trying to get pregnant.

Who Should Not Take CAMRESE?

Do not take CAMRESE if you:

- smoke and are over 35 years of age
- have or had blood clots in your arms, legs, eyes or lungs
- had a stroke
- had a heart attack
- have certain heart valve problems or heart rhythm abnormalities that can cause blood clots to form in the heart
- have or had a problem with your blood that makes it clot more than normal
- have high blood pressure that cannot be controlled by medicine or have high blood pressure with blood vessel problems
- have diabetes and are over the age of 35; have diabetes with high blood pressure; kidney, eye, nerve, or blood vessel damage; or for more than 20 years
- have certain kinds of severe migraine headaches with aura, numbness, weakness or changes in vision, or any migraine headaches if you are over the age of 35
- have or had breast cancer
- have liver disease, including liver tumors
- have unexplained vaginal bleeding
- take any Hepatitis C drug combination containing ombitasvir/paritaprevir/ritonavir, with or without dasabuvir. This may increase levels of the liver enzyme “alanine aminotransferase” (ALT) in the blood.
  Birth control pills may not be a good choice for you if you have ever had jaundice (yellowing of the skin or eyes) caused by pregnancy.
  If any of these conditions happen to you while you are taking CAMRESE, stop taking CAMRESE right away and talk to your healthcare provider. Use non-hormonal contraception when you stop taking CAMRESE.
  What should I tell my healthcare provider before taking CAMRESE?
  Tell your healthcare provider if you:
- are pregnant or think you may be pregnant
- are scheduled for surgery. CAMRESE may increase your risk of blood clots after surgery. You should stop taking CAMRESE at least 4 weeks before you have surgery and not restart CAMRESE until at least 2 weeks after your surgery.
- are depressed now or have been depressed in the past
- had yellowing of your skin or eyes (jaundice) caused by pregnancy (cholestasis of pregnancy)
- are breastfeeding or plan to breastfeed. CAMRESE may decrease the amount of breast milk you make. A small amount of the hormones in CAMRESE may pass into your breast milk. Talk to your healthcare provider about the best birth control method for you while breastfeeding.
  Tell your healthcare provider if you have ever had any of the conditions listed in, “Who should not take CAMRESE” above. Your healthcare provider may recommend another method of birth control.
  Tell your healthcare provider about all medicines and herbal products that you take. Some medicines and herbal products may make birth control pills less effective, including:
- barbiturates
- bosentan
- carbamazepine
- felbamate
- griseofulvin
- oxcarbazepine
- phenytoin
- rifampin
- St. John’s wort
- topiramate
  Use a backup or alternative birth control method when you take medicines that may make birth control pills less effective.
  Birth control pills may interact with lamotrigine, an anticonvulsant used for epilepsy. This may increase the risk of seizures, so your physician may need to adjust the dose of lamotrigine.
  Women on thyroid hormone replacement therapy may need increased doses of thyroid hormone.
  Know the medicines you take. Keep a list of them to show your healthcare provider and pharmacist when you get a new medicine.
  How should I take CAMRESE?
  Read the Instructions for Use at the end of this Patient Information.
  What are the most serious risks of taking birth control pills?
  Like pregnancy, birth control pills increase the risk of serious blood clots, especially in women who have other risk factors, such as smoking, obesity, or age over 35 years old. It is possible to die from a problem caused by a blood clot, such as a heart attack or a stroke. Some examples of serious blood clots are blood clots in the:
- Legs (thrombophlebitis)
- Lungs (pulmonary embolus)
- Eyes (loss of eyesight)
- Heart (heart attack)
- Brain (stroke)
  Women who take birth control pills may get:
- High blood pressure. You should see your healthcare provider to check your blood pressure regularly.
- Gallbladder problems
- Rare cancerous or noncancerous liver tumors
  All of these events are uncommon in healthy women.
  Call your healthcare provider right away if you have:
- Persistent leg pain
- Sudden shortness of breath
- Sudden blindness, partial or complete
- Severe pain in your chest
- Sudden, severe headache unlike your usual headaches
- Weakness or numbness in an arm or leg, or trouble speaking
- Yellowing of the skin or eyeballs
  What are common side effects of birth control pills?
  The most common side effects of birth control pills are:
- Spotting or bleeding between menstrual periods
- Nausea
- Breast tenderness
- Headache
  These side effects are usually mild and usually disappear with time.
  Less common side effects are:
- Acne
- Less sexual desire
- Bloating or fluid retention
- Blotchy darkening of the skin, especially on the face
- High blood sugar, especially in women who already have diabetes
- High fat levels in the blood
- Depression, especially if you have had depression in the past. Call your healthcare provider immediately if you have any thoughts of harming yourself.
- Problems tolerating contact lenses
- Weight changes

This is not a complete list of possible side effects. Talk to your healthcare provider if you develop any side effects that concern you. You may report side effects to the FDA at 1‑800-FDA-1088.

No serious problems have been reported from a birth control pill overdose, even when accidentally taken by children.

What else should I know about taking CAMRESE?

- If you are scheduled for any lab tests, tell your healthcare provider you are taking CAMRESE. Certain blood tests may be affected by CAMRESE.
- Do not skip any pills, even if you do not have sex often.
- Birth control pills should not be taken during pregnancy. However, birth control pills taken by accident during pregnancy are not known to cause birth defects.
- You should stop CAMRESE at least four weeks before you have major surgery and not restart it for at least two weeks after the surgery, due to an increased risk of blood clots.
- If you are breastfeeding, consider another birth control method until you are ready to stop breastfeeding. Birth control pills that contain estrogen, like CAMRESE, may decrease the amount of milk you make. A small amount of the pill's hormones pass into breast milk.
- If you have vomiting or diarrhea, your birth control pills may not work as well. Use another birth control method, like condoms or a spermicide, until you check with your healthcare provider.
  How should I store CAMRESE?
- Store CAMRESE at room temperature between 68°F to 77°F (20°C to 25°C).
- Keep CAMRESE and all medicines out of the reach of children.

General information about CAMRESE

Medicines are sometimes prescribed for purposes other than those listed in a Patient Information leaflet. Do not use CAMRESE for a condition for which it was not prescribed. Do not give CAMRESE to anyone else.

This Patient Information summarizes the most important information about CAMRESE. If you have concerns or questions, ask your healthcare provider. You may also ask your healthcare providers for a more detailed label written for medical professionals.

Do birth control pills cause cancer?

It is not known if hormonal birth control pills cause breast cancer. Some studies, but not all, suggest that there could be a slight increase in the risk of breast cancer among current users with longer duration of use.

If you have breast cancer now, or have had it in the past, do not use hormonal birth control because some breast cancers are sensitive to hormones. Women who use birth control pills may have a slightly higher chance of getting cervical cancer. However, this may be due to other reasons such as having more sexual partners.

What if I want to become pregnant?

You may stop taking the pill whenever you wish. Consider a visit with your healthcare provider for a pre-pregnancy checkup before you stop taking the pill.

What should I know about my period when taking CAMRESE?

When you take CAMRESE, which has a 91-day extended dosing cycle, you should expect to have 4 scheduled periods per year (bleeding when you are taking the 7 yellow pills). Each period is likely to last about 3 days. However, you will probably have more bleeding or spotting between your scheduled periods than if you were using a birth control pill with a 28-day dosing cycle. During the first CAMRESE 91-day treatment cycle, about 3 in 10 women may have 20 or more days of unplanned bleeding or spotting. This bleeding or spotting tends to decrease with time. Do not stop taking CAMRESE because of this bleeding or spotting. If the spotting continues for more than 7 consecutive days or if the bleeding is heavy, call your healthcare provider.

What if I miss my scheduled period when taking CAMRESE?

You should consider the possibility that you are pregnant if you miss your scheduled period (no bleeding on the days that you are taking yellow tablets). Since scheduled periods are less frequent when you are taking CAMRESE, notify your healthcare provider that you have missed your period and that you are taking CAMRESE. Also notify your healthcare provider if you have symptoms of pregnancy such as morning sickness or unusual breast tenderness. It is important that your healthcare provider evaluates you to determine if you are pregnant. Stop taking CAMRESE if it is determined that you are pregnant.

What are the ingredients in CAMRESE?

Active ingredients:

Light blue-green tablets: levonorgestrel and ethinyl estradiol

Yellow tablets: ethinyl estradiol

Inactive ingredients:

Light blue-green tablets: anhydrous lactose, D&C yellow no. 10 aluminum lake, FD&C blue no. 1 aluminum lake, FD&C yellow no. 6/Sunset yellow aluminum lake, hypromellose, lactose monohydrate, magnesium stearate, microcrystalline cellulose, titanium dioxide and triacetin.

Yellow tablets: anhydrous lactose, D&C yellow no. 10 aluminum lake, FD&C yellow no. 6/Sunset yellow aluminum lake, hypromellose, magnesium stearate, microcrystalline cellulose, polacrilin potassium, polyethylene glycol, polysorbate 80 and titanium dioxide.

INSTRUCTIONS FOR USE

CAMRESE

(levonorgestrel/ethinyl estradiol and ethinyl estradiol tablets)

How do I take CAMRESE?

1. Take one pill every day at the same time. If you miss pills you could get pregnant. This includes starting the pack late. The more pills you miss, the more likely you are to get pregnant.

2. Many women have spotting or light bleeding or may feel sick to their stomach during the first few months of taking CAMRESE. If you feel sick to your stomach, do not stop taking the pill. The problem will usually go away. If it doesn't go away, check with your healthcare provider.

3. Missing pills can also cause spotting or light bleeding, even when you take the missed pills later. On the days you take 2 pills to make up for missed pills, you could also feel a little sick to your stomach.

4. If you have trouble remembering to take CAMRESE, talk to your healthcare provider about how to make pill-taking easier or about using another method of birth control.

Before you start taking CAMRESE

1. Decide what time of day you want to take your pill. It is important to take it at about the same time every day.

2. Look at your Extended-Cycle Tablet Dispenser. Your Tablet Dispenser consists of 3 trays with cards that hold 91 individually sealed pills (a 13-week or 91-day cycle). The 91 pills consist of 84 light blue-green and 7 yellow pills. Trays 1 and 2 each contain 28 light blue-green pills (4 rows of 7 pills). Tray 3 contains 35 pills consisting of 28 light blue-green pills (4 rows of 7 pills) and 7 yellow pills (1 row of 7 pills).

3. Also find:

- Where on the first tray in the pack to start taking pills (upper left corner at the start arrow) and

- In what order to take the pills (follow the weeks and arrow).

4. Be sure you have ready at all times another kind of birth control (such as condoms or spermicide), to use as a backup in case you miss pills.

If you are switching from another birth control method:

If you have been using a different hormonal method of birth control (such as a different pill, the “patch,” or the “vaginal ring”), you need to use another method of birth control (such as condoms or spermicide) each time you have sex after stopping your old method of birth control until you have taken CAMRESE for 7 days.

If you have recently given birth and have not yet had a period, use another method of birth control if you have sex (such as condoms and spermicide) as a backup method until you have taken CAMRESE for 7 days.

When to start CAMRESE

1. Take the first light blue-green pill on the Sunday after your period starts, even if you are still bleeding. If your period begins on Sunday, start the first light blue-green pill that same day.

2. Use another method of birth control (such as condoms or spermicide) as a backup method if you have sex anytime from the Sunday you start your first light blue-green pill until the next Sunday (first 7 days). If you have been using a different hormonal method of birth control (such as a different pill, the “patch,” or the “vaginal ring”), you need to use another method of birth control (such as condoms or spermicide) each time you have sex after stopping your old method of birth control until you have taken CAMRESE for 7 days.

How to take CAMRESE

1. Take one pill at the same time every day until you have taken the last pill in the tablet dispenser.

- Do not skip pills even if you are experiencing spotting or bleeding or feel sick to your stomach (nausea).
- Do not skip pills even if you do not have sex very often.

2. When you finish a tablet dispenser

- After taking the last yellow pill, start taking the first light blue-green pill from a new Extended-Cycle Tablet Dispenser the very next day (this should be on a Sunday) regardless of when your period started.

3. If you miss your scheduled period when you are taking the yellow pills, contact your healthcare provider because you may be pregnant. If you are pregnant, you should stop taking CAMRESE.

What to do if you miss pills

If you MISS 1 light blue-green pill:

1. Take it as soon as you remember. Take the next pill at your regular time. This means you may take 2 pills in 1 day.

2. You do not need to use a backup birth control method if you have sex.

If you MISS 2 light blue-green pills in a row:

1. Take 2 pills on the day you remember, and 2 pills the next day.

2. Then take 1 pill a day until you finish the pack.

3. You could become pregnant if you have sex in the 7 days after you miss two pills. You MUST use another birth control method (such as condoms or spermicide) as a backup for the 7 days after you restart your pills.

If you MISS 3 OR MORE light blue-green pills in a row:

1. Do not take the missed pills. Keep taking 1 pill every day as indicated on the pack until you have completed all of the remaining pills in the pack. For example: If you resume taking the pill on Thursday, take the pill under “Thursday” and do not take the missed pills. You may experience bleeding during the week following the missed pills.

2. You could become pregnant if you have sex during the days of missed pills or during the first 7 days after restarting your pills.

3. You MUST use a non-hormonal birth control method (such as condoms or spermicide) as a backup when you miss pills and for the first 7 days after you restart your pills. If you do not have your period when you are taking the yellow pills, call your healthcare provider because you may be pregnant.

If you MISS ANY of the 7 yellow pills:

1. Throw away the missed pills.

2. Keep taking the scheduled pills until the pack is finished.

3. You do not need a backup method of birth control.

Finally, if you are still not sure what to do about the pills you have missed

- Use a backup method anytime you have sex.
- Keep taking one pill each day until you contact your healthcare provider.

This Patient Information and Instructions for Use has been approved by the U.S. Food and Drug Administration.

Manufactured for:
Teva Pharmaceuticals
Parsippany, NJ 07054

CAMPL-003

Revised: 10/2024

© 2024 Teva Pharmaceuticals, Inc.

Package/Label Display Panel, Part 1 of 2

Rx only

2 Extended-Cycle Tablet Dispensers,

91 Tablets Each

NDC 0093-3134-82

2 Extended-Cycle Tablet Dispensers

CAMRESE® levonorgestrel/ethinyl estradiol

0.15 mg/0.03 mg tablets and ethinyl estradiol 0.01 mg tablets

Contains 2 Extended-Cycle Tablet Dispensers, each containing 91 tablets: 84 light blue-green tablets, each containing 0.15 mg levonorgestrel with 0.03 mg ethinyl estradiol, and 7 yellow tablets, each containing 0.01 mg ethinyl estradiol.

Manufactured for:
Teva Pharmaceuticals
Parsippany, NJ 07054

TEVA